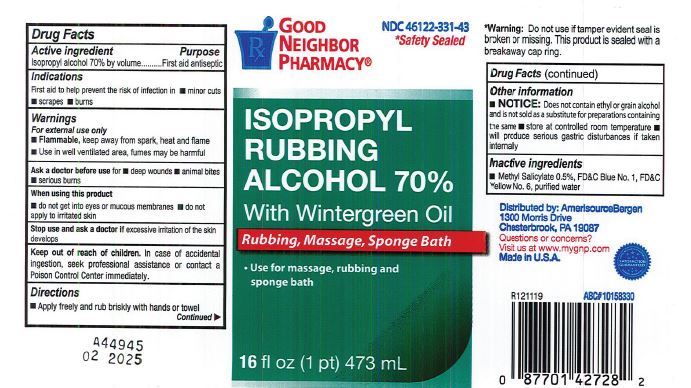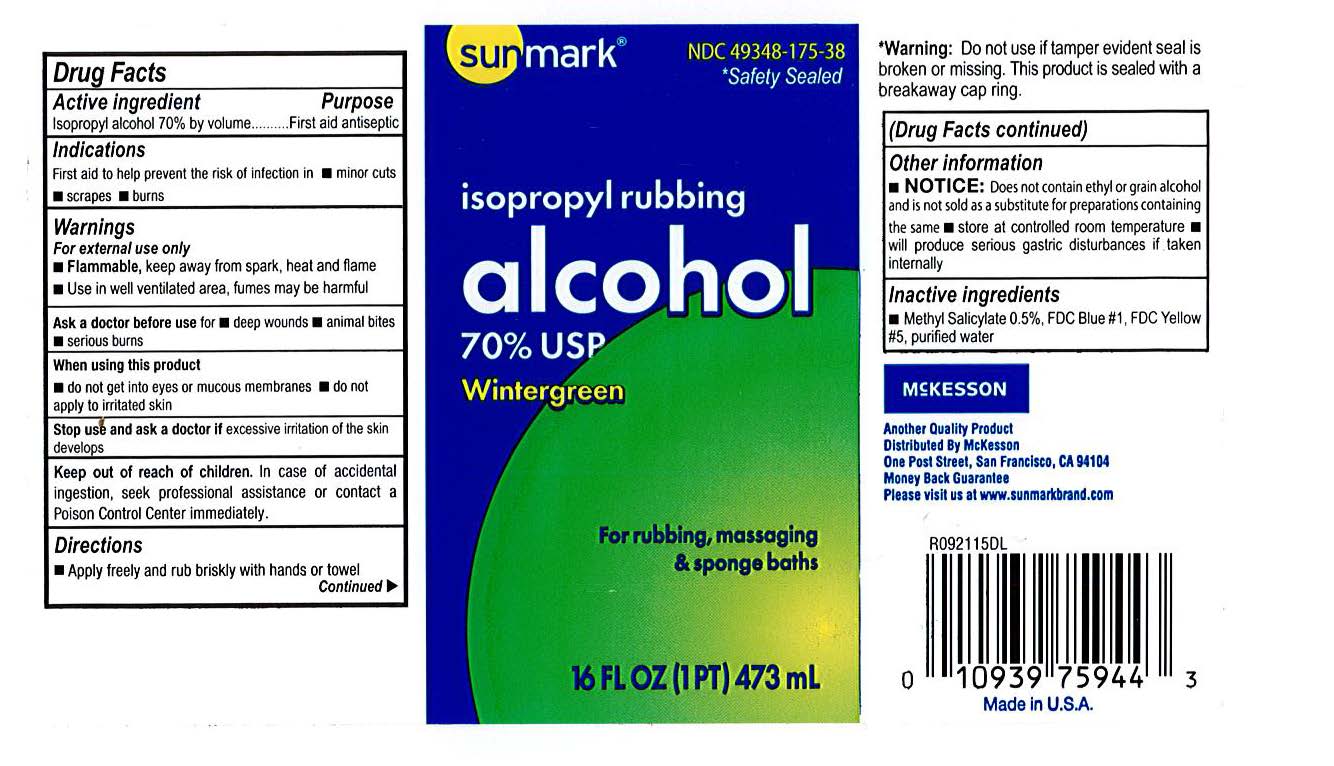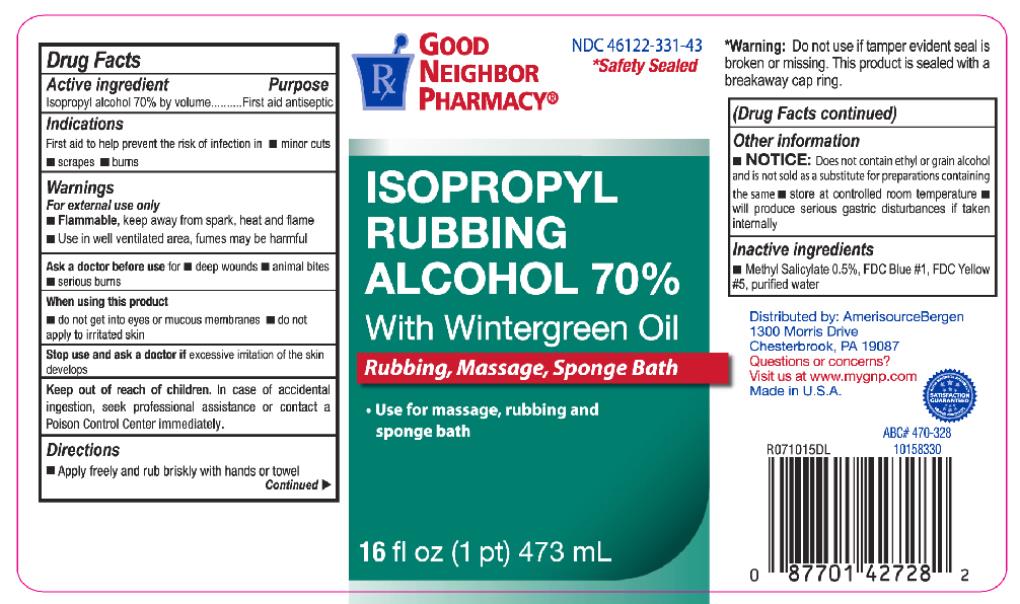 DRUG LABEL: Isopropyl Alcohol 70 Percent With Wintergreen Oil
NDC: 82645-915 | Form: LIQUID
Manufacturer: Pharma Nobis, LLC
Category: otc | Type: HUMAN OTC DRUG LABEL
Date: 20231226

ACTIVE INGREDIENTS: ISOPROPYL ALCOHOL 700 mg/1 mL
INACTIVE INGREDIENTS: METHYL SALICYLATE; FD&C BLUE NO. 1; FD&C YELLOW NO. 5; WATER

Private Label Isopropyl Alcohol 70 Percent, USP With Wintergreen Oil

Drug Facts

Active Ingredient

Isopropyl Alcohol 70% by volume

Purpose

First aid antiseptic

Use

First aid to help prevent the risk of infection in.

- minor cuts
- scrapes
- burns

Warnings

For external use only.

- Flammable, keep way from spark, heat and flame.
- Use in well ventilated area, fumes may be harmful.

Ask a doctor before use for

- deep wounds
- animal bites
- serious burns

When using this product

- do not get into eyes or mucous membranes.
- do not apply to irritated skin.

Stop use and ask a doctor if

excessive irritation of the skin develops.

Keep out of reach of children.

In case of accidental ingestion, seek professional assistance or contact a Poison Control Center immediately.

Directions

- apply freely and rub briskly with hands or towel.

Other Information

- does not contain ethyl or grain alcohol and is not sold as a substitute for preparations containing the same.
- Store at controlled room temperature
- will produce serious gastric disturbances if taken internally.

Inactive Ingredient

Methyl salicylate 0.5%

FDC Blue #1

FDC Yellow #5

purified water